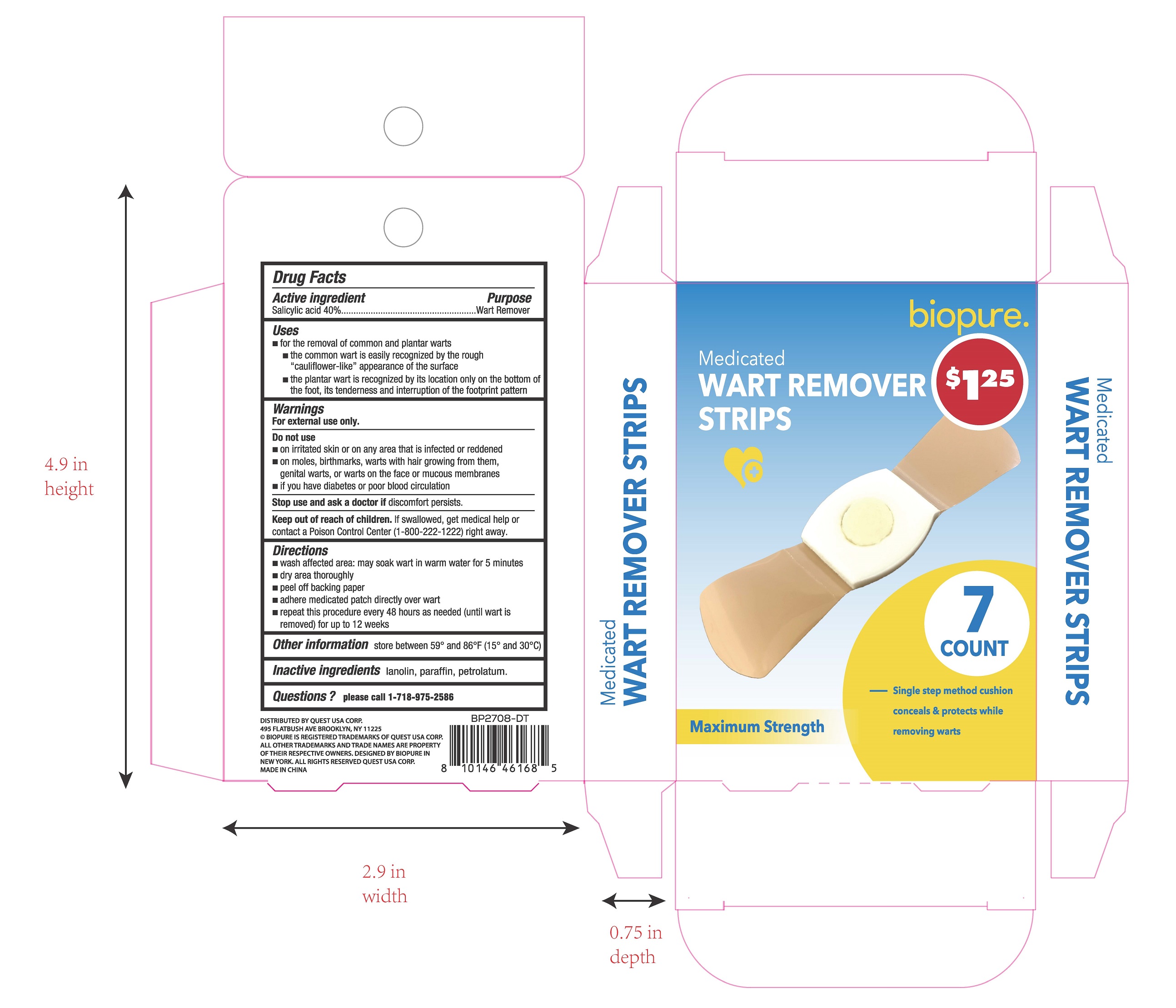 DRUG LABEL: Biopure Medicated Wart Remover Strips
NDC: 69070-308 | Form: PLASTER
Manufacturer: Zhejiang Dingtai Pharmaceutical Co., Ltd
Category: otc | Type: HUMAN OTC DRUG LABEL
Date: 20240502

ACTIVE INGREDIENTS: SALICYLIC ACID 0.4 g/1 g
INACTIVE INGREDIENTS: PARAFFIN; PETROLATUM; LANOLIN

Active ingredient

Salicylic Acid 40%

Purpose

Wart Remover

Uses

- for the removal of common plantar warts
- the common wart is easily recognized by the rough "cauliflower-like" appearance of the surface
- the plantar wart is recognized by its location only on the bottom of the foot, its tenderness and interruption of the footprint pattern

Warnings

For external use only.

Stop use and ask a doctor if

discomfort persists.

Do not use

on irritated skin or on any area that is infected or reddened

on moles, birthmarks, warts with hair growing from them, genital warts, or warts on the face or mucous membranes

if you have diabetes or poor blood circulation

Keep out of reach of children. If swallowed, get medical help or contact a Poison Control Center (1-800-222-1222) right away.

Directions

- wash affected area: may soak wart in warm water for 5 minutes
- dry area thoroughly
- peel off backing paper
- adhere medicated patch directly over wart
- repeat this procedure every 48 hours as needed (until wart is removed) for up to 12 weeks

Other information

store between 59º and 86°F (15º and 30ºC)

Inactive ingredients

lanolin, paraffin, petrolatum

Questions?

please call 1-718-975-2586